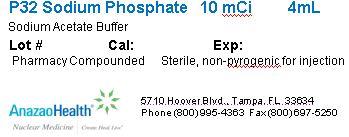 DRUG LABEL: P32 Sodium Phosphate
NDC: 51808-128 | Form: SOLUTION
Manufacturer: AnazaoHealth Corporation
Category: prescription | Type: HUMAN PRESCRIPTION DRUG LABEL
Date: 20120619

ACTIVE INGREDIENTS: PHOSPHORUS P-32 10 mCi/4 mL
INACTIVE INGREDIENTS: SODIUM ACETATE

P32 Sodium Phosphate

Dear Medical Professional,

Per your order, we have compounded P32 Sodium Phosphate as a sterile intravenous solution dispensed in a 10 mL plastic vial with a total volume of 4 mL. The characteristics of this preparation are described below.

DESCRIPTION

AnazaoHealth’s compounded P32 sodium phosphate vial is a sterile, non-pyrogenic radiopharmaceutical. The intravenous solution contains 0.25 N sodium acetate buffer, which is made of 0.9% sodium chloride and 0.09% sodium phosphate dibasic, and is compounded to a total volume of 4 mL. The pH of the solution is between 5 and 6.

INDICATIONS AND USAGE

P32 sodium phosphate is indicated for the treatment of polycythemia vera and is effective for the treatment of chronic myelocytic leukemia and chronic lymphocytic leukemia. It may also be used in the palliative treatment of selected patients with multiple areas of skeletal metastases

Mechanism of Action

Radioactive phosphorous concentrates to a very high degree in rapidly proliferating tissues

CONTRAINDICATIONS

P32 sodium phosphate should not be used as part of a sequential treatment with a chemotherapeutic agent. It should not be administered when the leukocyte count is below 5,000/cu mm or a platelet count that is below 150,000/cu mm.

In chronic myelocytic leukemia, it should not be administered when the leukocyte count is below 20,000/cu mm.

For the treatment of bone metastases, it is usually not administered when the leukocyte count is below 5,000/ cu mm and platelet count is below 100,000/cu mm

DOSAGE AND ADMINISTRATION

For polycythemia vera, intravenous dosages from 1 to 8 mCi are usually given depending upon the stage of disease and the size of the patient. Repeat doses must be adjusted to individual needs. For chronic leukemia, the individual dose is 6 to 15 mCi, usually administered with concomitant hormone manipulation

PACKAGE LABEL.PRINCIPAL DISPLAY PANEL

Figure 1